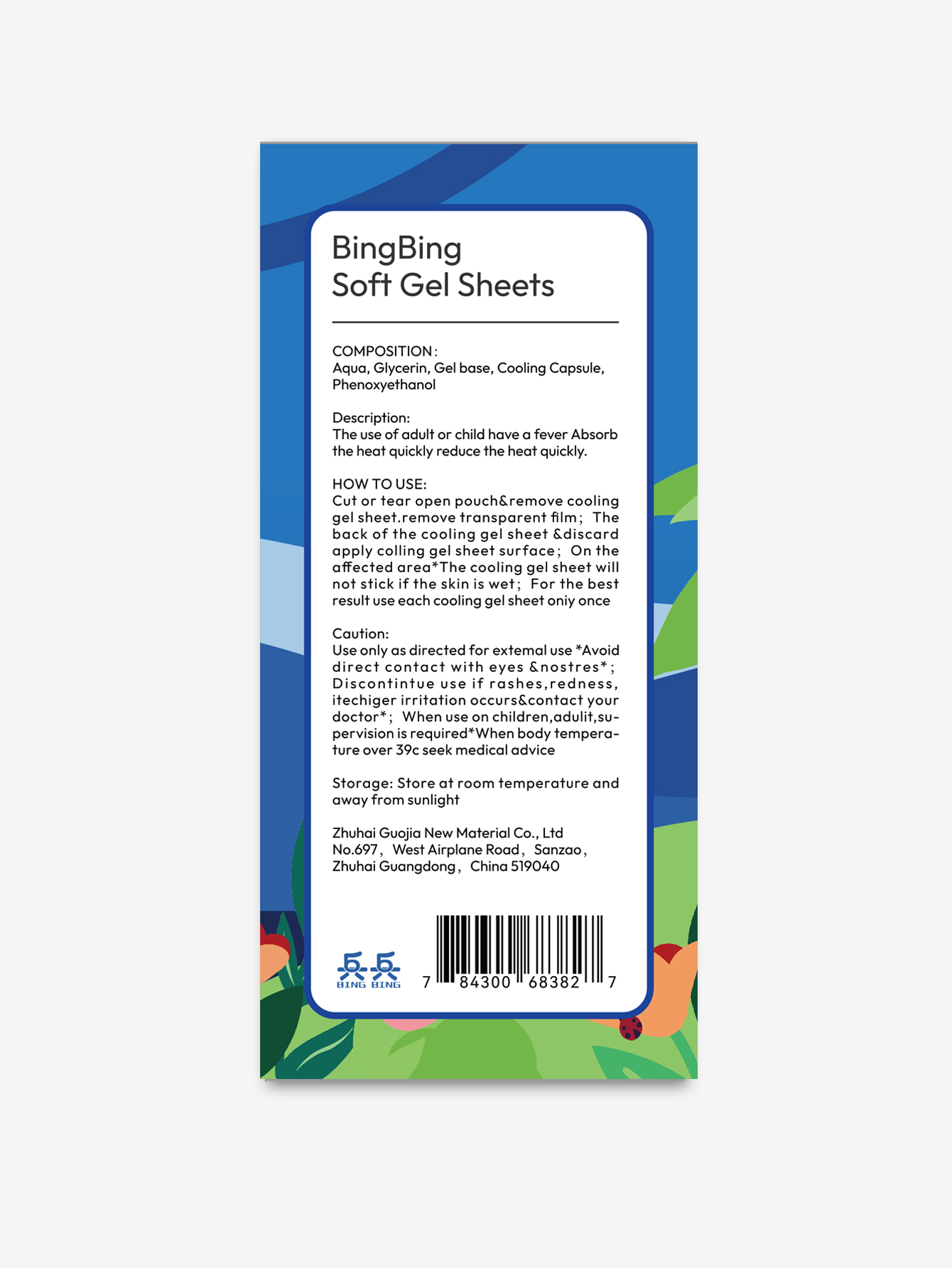 DRUG LABEL: fever relief patch
NDC: 84434-008 | Form: GEL
Manufacturer: Zhuhai Guojia International Trading Co., Ltd.
Category: otc | Type: HUMAN OTC DRUG LABEL
Date: 20240801

ACTIVE INGREDIENTS: PEPPERMINT OIL 2 g/64 cm2
INACTIVE INGREDIENTS: WATER; PHENOXYETHANOL; GLYCERIN

Inactive

water

Glycerin

Gel base

Phenoxyethanol

Purpose

QULCK ACTING
NO REFRIGERATION NEEDED
LONG-LASTING

Warning

Caution:
Use only as directed for extemal use *Avoiddirect contact with eyes &nostres*;Discontintue useifrashes,redness.itechigerirritation occurs&contact yourdoctor*; When use on children,adulit,su-pervisionis required*When body tempera-ture over 39c seek medical advice

inforamtion

Avoiddirect contact with eyes &nostres*,Discontintue useifrashes,redness.itechiger irritation occurs&contact your doctor

stop to use

Avoiddirect contact with eyes &nostres*,Discontintue useifrashes,redness.itechiger irritation occurs&contact your doctor

when

When use on children,adulit,su-pervisionis required*When body tempera-ture over 39c seek medical advice

Storage

Storage: Store at room temperature andaway from sunlight and out of children

HOW TO USE:Cut or tear open pouch&remove coolinggel sheet.remove transparent flm; Theback of the cooling gel sheet &discardapply colling gel sheet surface; On theaffected area*The cooling gel sheet willnot stick if the skin is wet; For the bestresult use each cooling gel sheet oniy once

Dosage

1pc one time

PACKAGE LABEL

Description:The use of adult or child have a fever Absorbthe heat quickly reduce the heat quickly.
HOW TO USE:Cut or tear open pouch&remove coolinggelsheet.remove transparent flm;Theback of the cooling gel sheet &discardapply colling gel sheet surface; On theaffected area*The cooling gel sheet willnot stick if the skin is wet; For the bestresult use each cooling gel sheet oniy once
Caution:Use only as directed for extemal use *Avoiddirect contact with eyes &nostres*;Discontintueuseifrashes,rednessitechigerirritation occurs&contact yourdoctor*; When use on children,adulit,su-pervision is required*When body tempera-ture over 39c seek medical advice
Storage: Store at room temperature andaway from sunlight